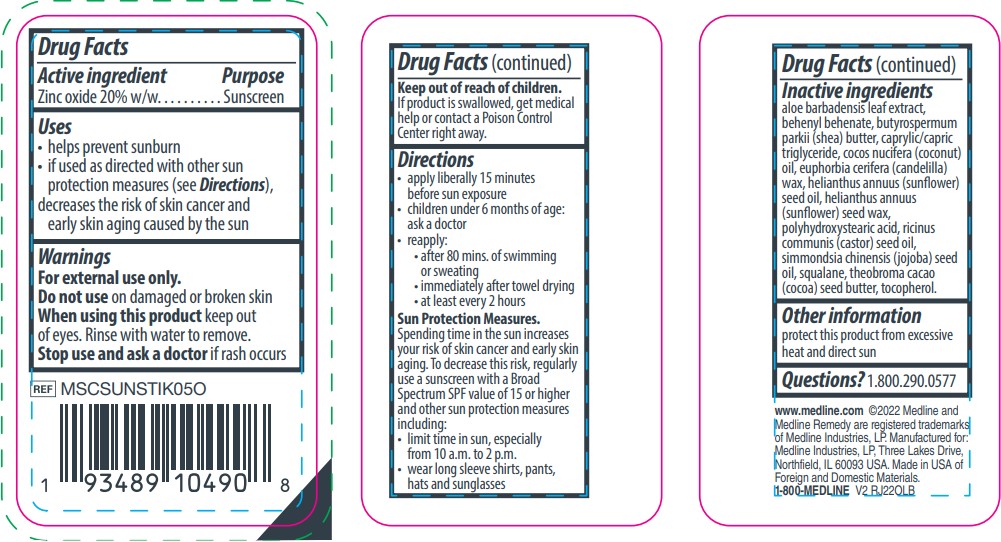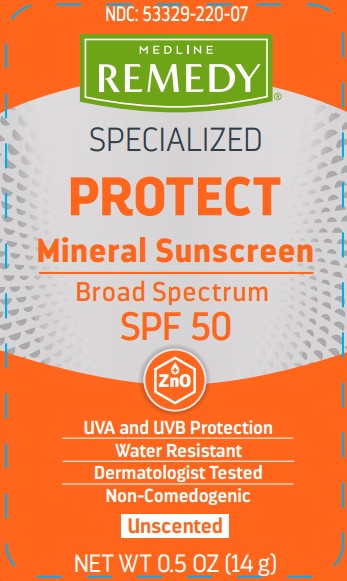 DRUG LABEL: Medline
NDC: 53329-220 | Form: STICK
Manufacturer: Medline Industries, LP
Category: otc | Type: HUMAN OTC DRUG LABEL
Date: 20251104

ACTIVE INGREDIENTS: ZINC OXIDE 20 g/100 g
INACTIVE INGREDIENTS: BEHENYL BEHENATE; CANDELILLA WAX; HELIANTHUS ANNUUS SEED WAX; SQUALANE; SHEA BUTTER; JOJOBA OIL; POLYHYDROXYSTEARIC ACID (2300 MW); CASTOR OIL; COCOA BUTTER; ALOE VERA LEAF; MEDIUM-CHAIN TRIGLYCERIDES; COCONUT OIL; SUNFLOWER OIL; TOCOPHEROL

220 RemedySunscreen Stick

Active ingredient

Zinc oxide 20% w/w

Purpose

Sunscreen

Uses

- helps prevent sunburn
- if used as directed with other sun protection measures (see Directions), decreases the risk of skin cancer and early skin aging caused by the sun

Warnings

For external use only.

Do not use

on damaged or broken skin

When using this product

keep out of eyes. Rinse with water to remove.

Stop use and ask a doctor

if rash occurs

Keep out of reach of children.

If product is swallowed, get medical help or contact a Poison Control Center right away.

Directions

- apply liberally 15 minutes before sun exposure
- children under 6 months of age: ask a doctor
- reapply:
- after 80 mins. of swimming or sweating
- immediately after towel drying
- at least every 2 hours

Sun Protection Measures.

Spending time in the sun increases your risk of skin cancer and early skin aging. To decrease this risk, regularly use a sunscreen with a Broad Spectrum SPF value of 15 or higher and other sun protection measures including:

- limit time in sun, especially from 10 a.m. to 2 p.m.
- wear long sleeve shirts, pants, hats and sunglasses

Inactive ingredients

aloe barbadensis leaf extract, behenyl behenate, butyrospermum parkii (shea) butter, caprylic/capric triglyceride, cocos nucifera (coconut) oil, euphorbia cerifera (candelilla) wax, helianthus annuus (sunflower) seed oil, helianthus annuus (sunflower) seed wax, polyhydroxystearic acid, ricinus communis (castor) seed oil, simmondsia chinensis (jojoba) seed oil, squalane, theobroma cacao (cocoa) seed butter, tocopherol

Other information

protect this product from excessive heat and direct sun

Questions?

1.800.290.0577

Manufacturing Information

www.medline.com

©2022 Medline and Medline Remedy are registered trademarks of Medline Industries, LP.

Manufactured for: Medline industries, LP, Three Lakes Drive, Northfield, IL 60093 USA

Made in USA of Foreign and Domestic Materials

1-800-MEDLINE

REF: MSCSUNSTIK05O